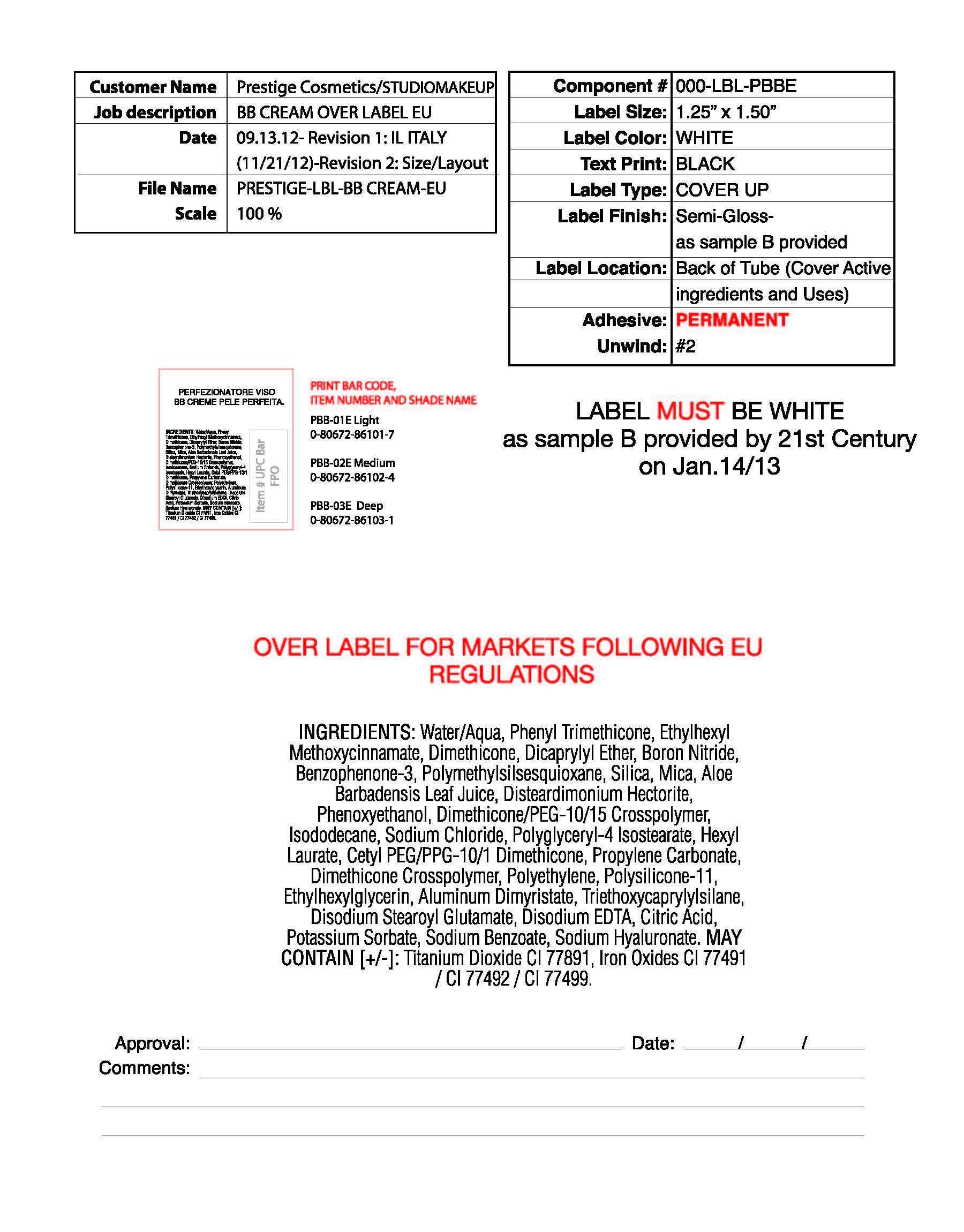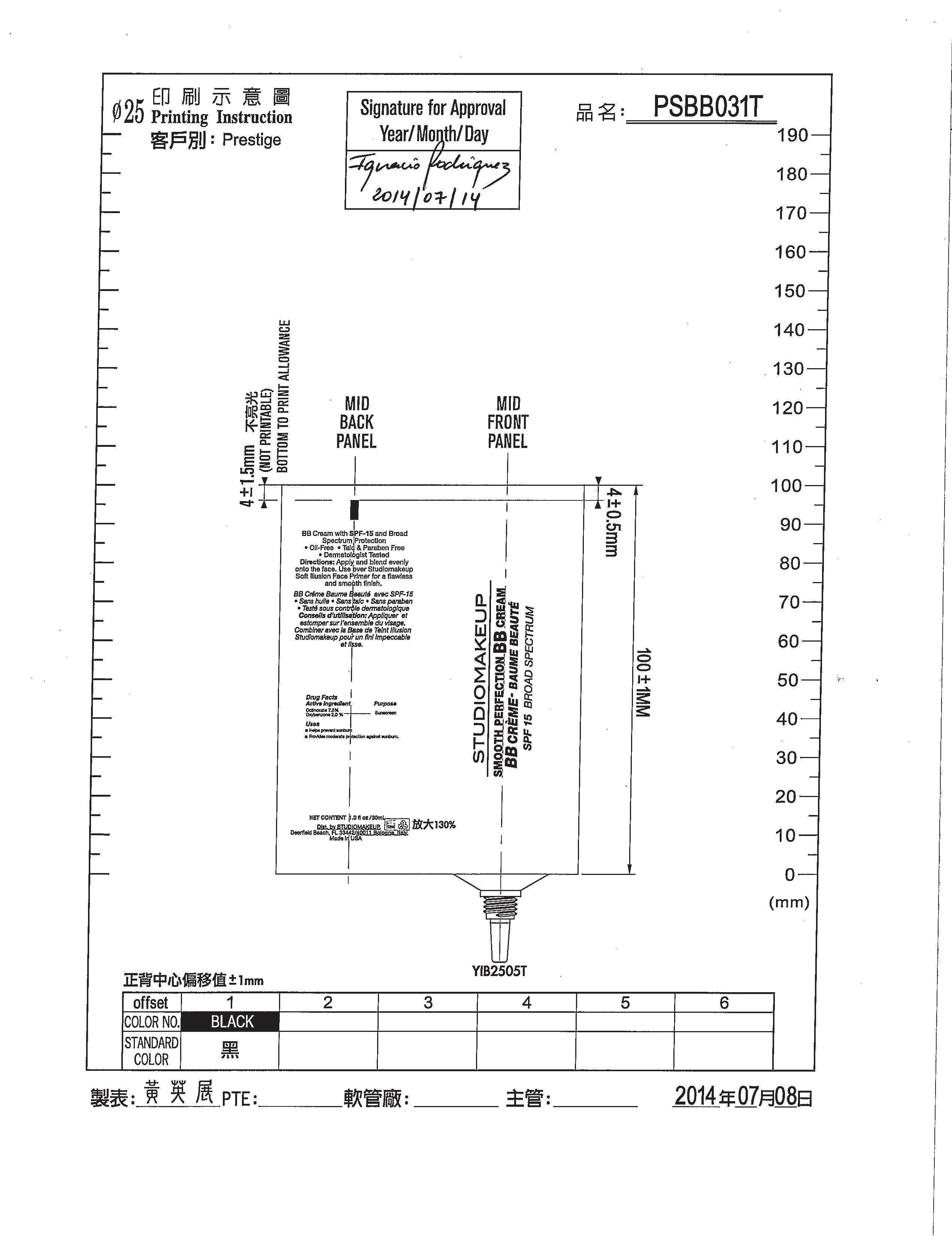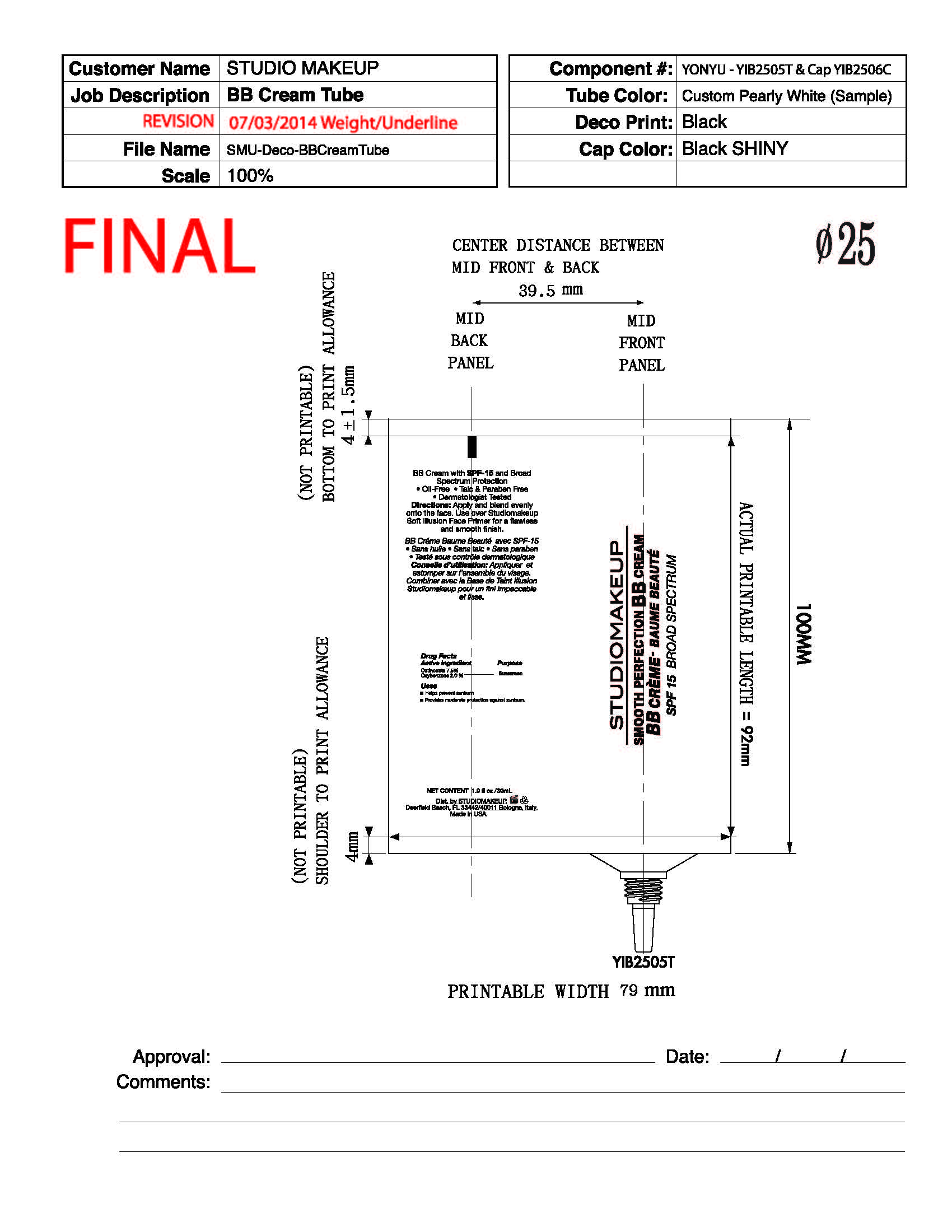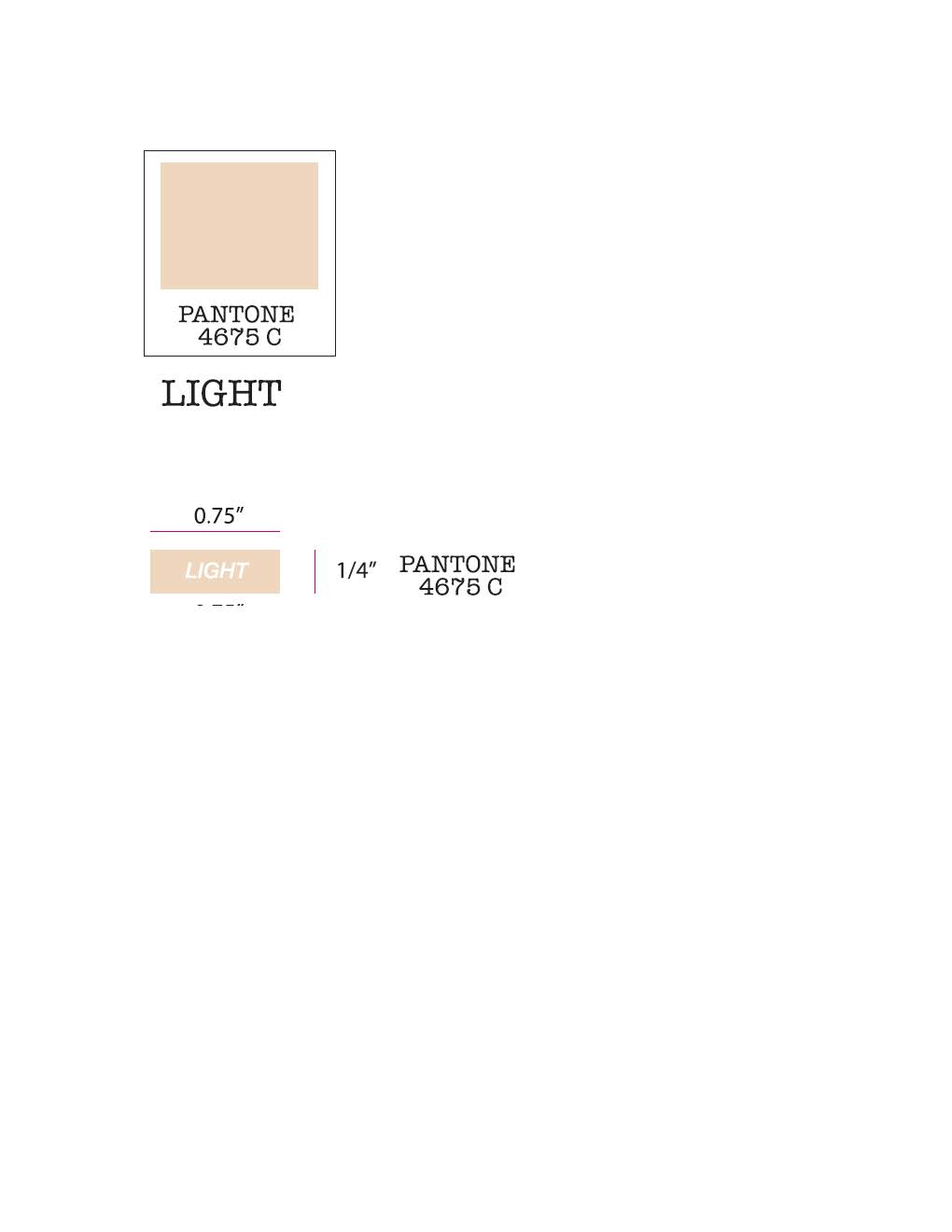 DRUG LABEL: cream
NDC: 61354-025 | Form: CREAM
Manufacturer: Oxygen Development
Category: otc | Type: HUMAN OTC DRUG LABEL
Date: 20230210

ACTIVE INGREDIENTS: OXYBENZONE 2 mg/100 mg; OCTINOXATE 7.49 mg/100 mg
INACTIVE INGREDIENTS: DIMETHICONE; PHENYL TRIMETHICONE; SODIUM CHLORIDE; SILICON DIOXIDE; PHENOXYETHANOL; ALOE VERA LEAF; WATER; ISODODECANE; DIMETHICONE/PEG-10/15 CROSSPOLYMER; DISTEARDIMONIUM HECTORITE; POLYMETHYLSILSESQUIOXANE (4.5 MICRONS); MICA; DICAPRYLYL ETHER; BORON NITRIDE

Studiomakeup smooth perfection BB cream SPF 15 broad spectrum

Active Ingredient

Octinoxate 7.5

Oxybenzone 2.0

Purpose

Sunscreen

Uses

helps prevent sunburn. Provides moderate protection against sunburn.

Directions

Apply and blend evenly onto the face. Use over Studiomakeup soft illusion Face Primer for a flawless and smooth finish

Ingredients

Water/Aqua, phenyl trimethicone, ethylhexyl methoxycinnamate, dimethicone, dicaprylyl ether, boron nitride, benzophenone-3, polymethylsilsesquioxane, silica, mica, aloe barbadensis leaf juice, disteardimonium hectorite, phenoxyethanol, dimethicone/PEG-10/15 crosspolymer, isododecane, sodium chloride, polyglyceryl-4 isostearate, hexyl laurate, cetyl PEG/PPG-10/1 dimethicone, propylene carbonate, dimethicone crosspolymer, polyethylene, polysilicone-11, ethylhexyglycerin, aluminum dimyristate, triehoxycaprylylsilane,disodium stearoyl glutamate, disodium EDTA, citric acid, potassium sorbate, sodium benzoate, sodium hyaluronate. May contain [+/-]: titanium dioxide CI 77891, iron oxides CI 77491/ CI 77492/ CI 77499